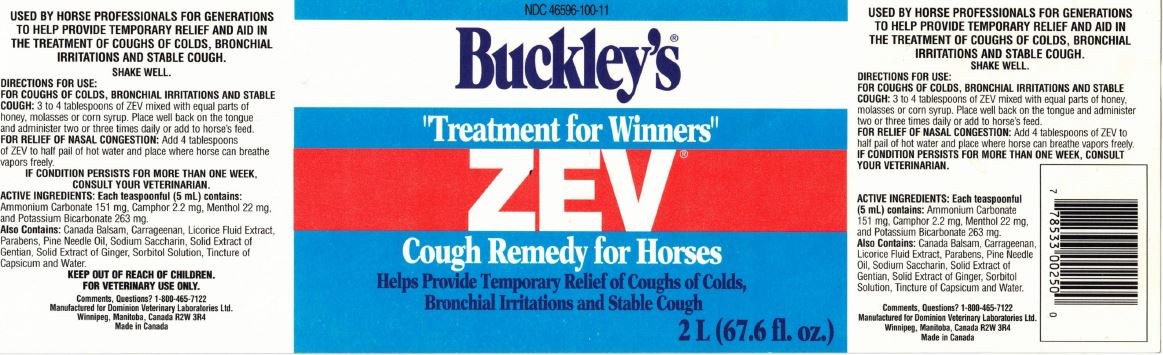 DRUG LABEL: ZEV COUGH REMEDY FOR HORSES
NDC: 64120-100 | Form: SOLUTION
Manufacturer: DOMINION VETERINARY LABORATORIES LTD.
Category: animal | Type: OTC ANIMAL DRUG LABEL
Date: 20211110

ACTIVE INGREDIENTS: AMMONIUM CARBONATE 151 mg/5 mL; CAMPHOR OIL 2.2 mg/5 mL; MENTHOL 22 mg/5 mL; POTASSIUM BICARBONATE 263 mg/5 mL
INACTIVE INGREDIENTS: CANADA BALSAM; CARRAGEENAN; LICORICE; PROPYLPARABEN; PINE NEEDLE OIL (PINUS SYLVESTRIS); SACCHARIN SODIUM; GENTIANA LUTEA ROOT; GINGER; SORBITOL; CAPSICUM; WATER

DOMINION VETERINARY LABORATORIES - ZEV COUGH REMEDY FOR HORSES

INDICATIONS:

TO HELP PROVIDE TEMPORARY RELIEF AND AID IN THE TREATMENT OF COUGHS OF COLDS, BRONCHIAL IRRITATIONS AND STABLE COUGH.